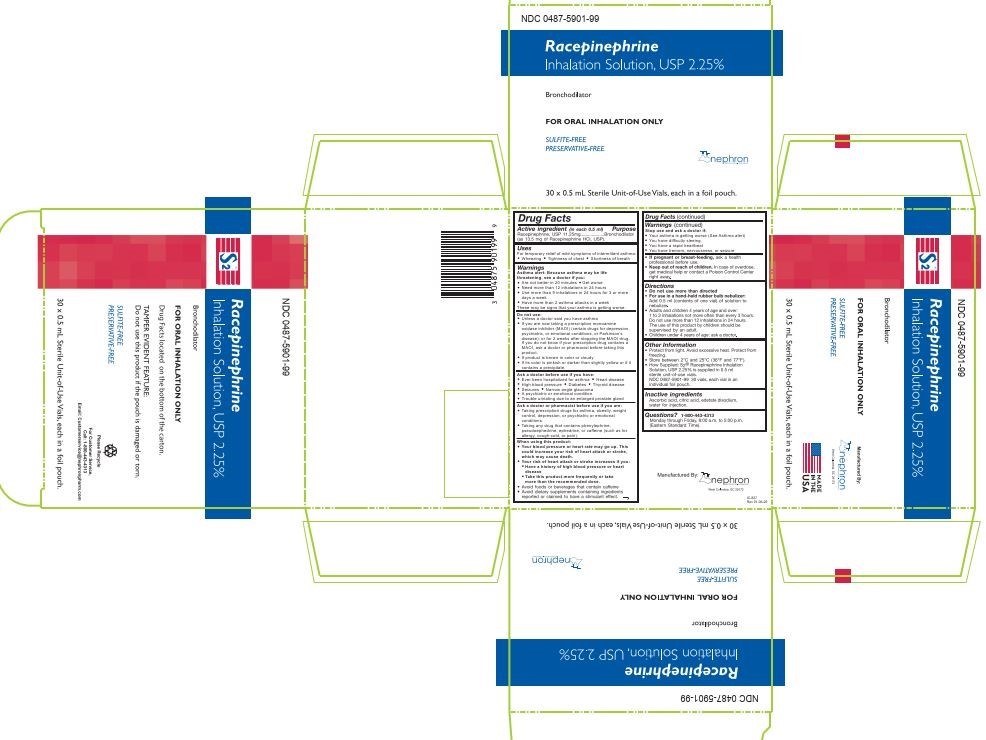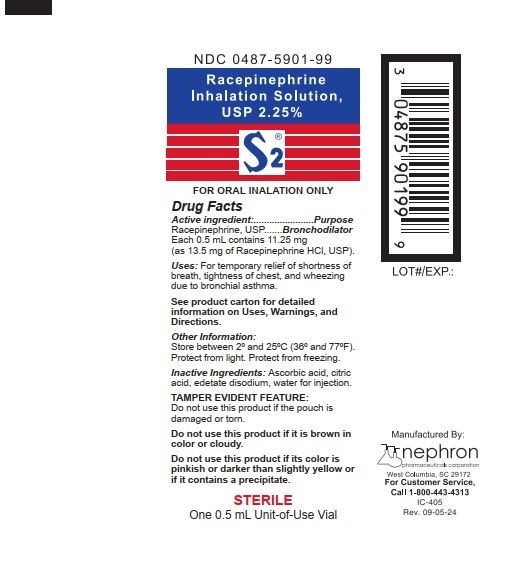 DRUG LABEL: S2
NDC: 0487-5901 | Form: SOLUTION
Manufacturer: Nephron Pharmaceuticals Corporation
Category: otc | Type: HUMAN OTC DRUG LABEL
Date: 20260126

ACTIVE INGREDIENTS: RACEPINEPHRINE HYDROCHLORIDE 11.25 mg/0.5 mL
INACTIVE INGREDIENTS: ASCORBIC ACID; CITRIC ACID MONOHYDRATE; EDETATE DISODIUM; WATER

Racepinephrine Inhalation Solution, USP 2.25%

Drug Facts

Active ingredient (in each 0.5 ml)

Racepinephrine, USP 11.25 mg (as 13.5 mg of Racepinephrine HCl, USP).

Purpose

Bronchodilator

Uses

For temporary relief of mild symptoms of intermittent asthma:

- Wheezing
- Tightness of chest
- Shortness of breath

Warnings

Asthma alert

Because asthma may be life threatening, see a doctor if you:

- Are not better in 20 minutes
- Get worse
- Need more than 12 inhalations in 24 hours
- Use more than 9 inhalations in 24 hours for 3 or more days a week
- Have more than 2 asthma attacks in a week

These may be signs that your asthma is getting worse.

Do not use:

- Unless a doctor said you have asthma
- If you are now taking a prescription monoamine oxidase inhibitor (MAOI) (certain drugs for depression, psychiatric, or emotional conditions, or Parkinson's disease), or for 2 weeks after stopping the MAOI drug. If you do not know if your prescription drug contains a MAOI, ask a doctor or pharmacist before taking this product.
- If product is brown in color or cloudy
- If its color is pinkish or darker than slightly yellow or if it contains a precipitate.

Ask a doctor before use if you have:

- Ever been hospitalized for asthma
- Heart disease
- High blood pressure
- Diabetes
- Thyroid disease
- Seizures
- Narrow angle glaucoma
- A psychiatric or emotional condition
- Trouble urinating due to an enlarged prostate gland

Ask a doctor or pharmacist before use if you are:

- Taking prescription drugs for asthma, obesity, weight control, depression, or psychiatric or emotional conditions.
- Taking any drug that contains phenylephrine, pseudoephedrine, ephedrine, or caffeine (such as for allergy, cough-cold, or pain).

Stop use and ask a doctor if:

- Your asthma is getting worse (See Asthma alert)
- You have difficulty sleeping
- You have a rapid heartbeat
- You have tremors, nervousness, or seizure

When using this product:

Your blood pressure or heart rate may go up. This could increase your risk of heart attack or stroke, which may cause death.

- Your risk of heart attack or stroke increases if you:
  - Have a history of high blood pressure or heart disease
  - Take this product more frequently or take more than the recommended dose.
  - Avoid foods or beverages that contain caffeine
  - Avoid dietary supplements containing ingredients reported or claimed to have a stimulant effect.

PREGNANCY OR BREAST FEEDING

- If pregnant or breast-feeding, ask a health professional before use.

- Keep out of reach of children. In case of overdose, get medical help or contact a Poison Control Center right away.

Directions

- The ingredient is used in an aqueous solution at a concentration equivalent to 1 percent epinephrine.
- Do not use more than directed
- For use in a hand-held rubber bulb nebulizer:
  Add 0.5 ml (contents of one vial) of solution to nebulizer.
- Adults and children 4 years of age and over:
  1 to 3 inhalations not more often than every 3 hours.
  Do not use more than 12 inhalations in 24 hours.
  The use of this product by children should be supervised by an adult.
- Children under 4 years of age: ask a doctor.

Other Information

- Protect from light. Avoid excessive heat. Protect from freezing.
- Store between 2°C and 25°C (36°F and 77°F).
- How Supplied: S2® Racepinephrine Inhalation Solution, USP 2.25% is supplied in 0.5 ml sterile unit-of-use vials.
  NDC 0487-5901-99 30 vials, each vial in an individual foil pouch.

Inactive Ingredients

Ascorbic acid, citric acid, edetate disodium, water for injection.

Questions?

1-800-443-4313

Monday through Friday, 8:00 a.m. to 5:00 p.m. (Eastern Standard Time).

Manufactured By:
Nephron Pharmaceuticals Corporation
West Columbia, SC 29172

PACKAGE LABEL, PRINCIPAL DISPLAY PANEL

Principle Display - Pouch Label (Individually Wrapped Vial)

NDC 0487-5901-99

Principle Display - Carton (30 Individually Wrapped Vials)

NDC 0487-5901-99